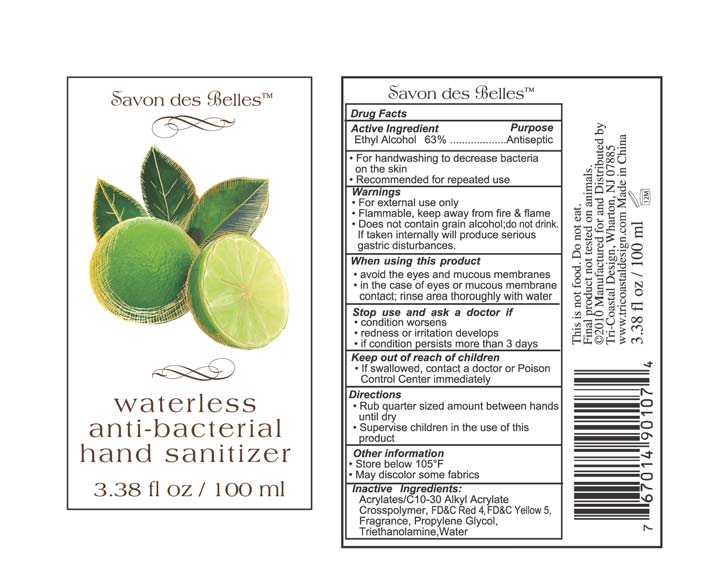 DRUG LABEL: waterless anti bacterial hand sanitizer
NDC: 49852-032 | Form: LIQUID
Manufacturer: Tri-Coastal Design Company Inc. 
Category: otc | Type: HUMAN OTC DRUG LABEL
Date: 20100715

ACTIVE INGREDIENTS: ALCOHOL 63 mL/100 mL
INACTIVE INGREDIENTS: CARBOMER COPOLYMER TYPE A; FD&C RED NO. 4; FD&C YELLOW NO. 5; PROPYLENE GLYCOL; TROLAMINE; WATER

Drug Facts

Active Ingredient

Ethyl Alcohol 63%

Purpose

Antiseptic

Uses

- For handwashing to decrease bacteria on the skin
- Recommended for repeated use

Warnings

- For external use only
- Flammable, keep away from fire and flame
- Does not contain grain alcohol; do not drink, if taken internally will produce serious gastric disturbances

When using this product

- avoid the eyes an mucous membranes
- in the case of eyes or mucous membrane contact; rinse area thoroughly with water

Stop use and ask a doctor if

- condition worsens
- redness or irritation develops
- if condition persists for more than 3 days

Keep out of reach of children

If swallowed contact a doctor or Poison Control Center immediately.

Directions

- Rub quarter sized amount between hands until dry
- Supervise children in the use of this product

Other information

- Store below 105F
- May discolor some fabrics

Inactive Ingredients

Acrylates/C10-30 Alkyl Acrylate Crosspolymer, FDC Red 4, FDC Yellow 5, Fragrance, Propylene Glycol, Triethanolamine, Water

Package Label